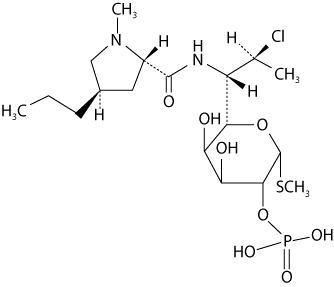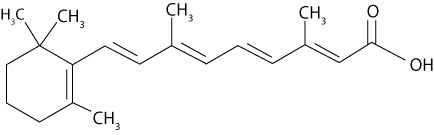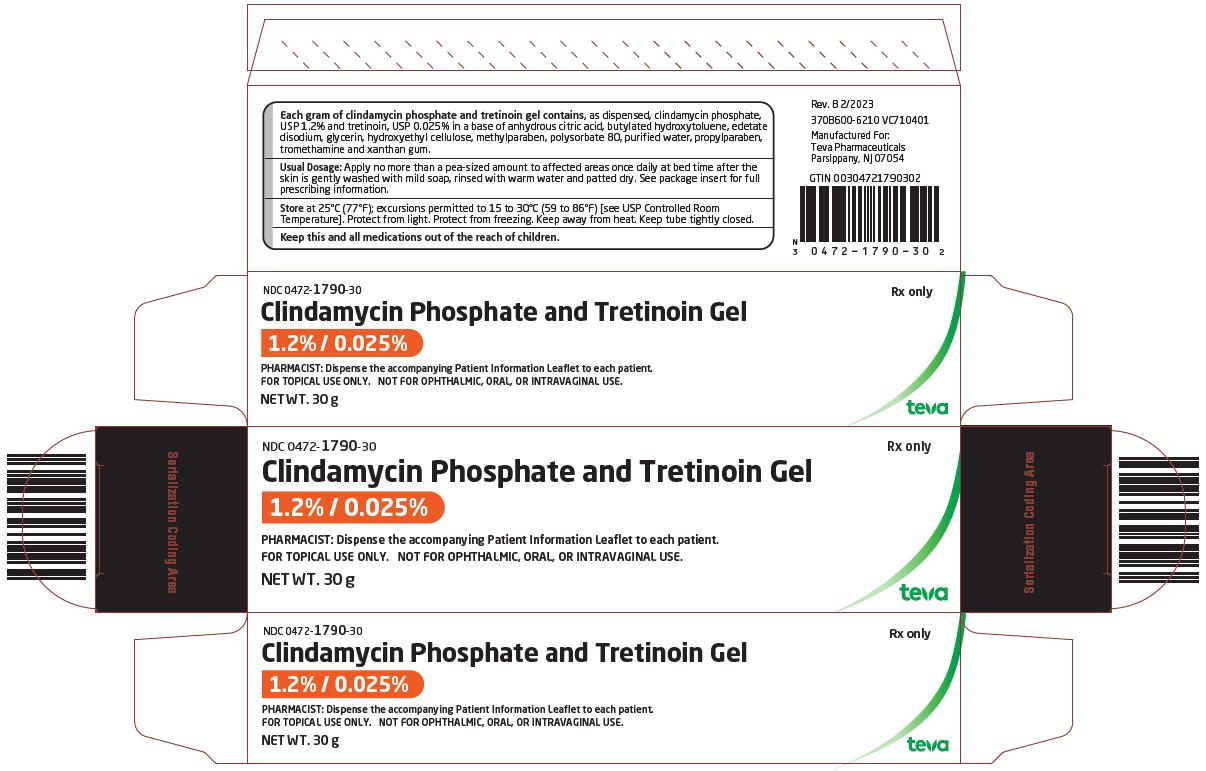 DRUG LABEL: Clindamycin Phosphate and Tretinoin
NDC: 0472-1790 | Form: GEL
Manufacturer: Actavis Pharma, Inc.
Category: prescription | Type: HUMAN PRESCRIPTION DRUG LABEL
Date: 20230227

ACTIVE INGREDIENTS: CLINDAMYCIN PHOSPHATE 12 mg/1 g; TRETINOIN 0.25 mg/1 g
INACTIVE INGREDIENTS: ANHYDROUS CITRIC ACID; BUTYLATED HYDROXYTOLUENE; EDETATE DISODIUM; HYDROXYETHYL CELLULOSE (100 MPA.S AT 2%); GLYCERIN; METHYLPARABEN; POLYSORBATE 80; PROPYLPARABEN; WATER; TROMETHAMINE; XANTHAN GUM

HIGHLIGHTS OF PRESCRIBING INFORMATION

These highlights do not include all the information needed to use clindamycin phosphate and tretinoin gel 1.2% / 0.025% safely and effectively. See full prescribing information for clindamycin phosphate and tretinoin gel 1.2% / 0.025%.
CLINDAMYCIN PHOSPHATE and TRETINOIN Gel 1.2% / 0.025%, for topical use only
Initial U.S. Approval: 2006

1 INDICATIONS AND USAGE

Clindamycin phosphate and tretinoin gel 1.2% / 0.025% is a lincosamide antibiotic and retinoid combination product indicated for the topical treatment of acne vulgaris in patients 12 years or older. (1)

2 DOSAGE AND ADMINISTRATION

- Apply a pea-sized amount to the entire face once daily at bedtime. Do not apply to eyes, mouth, angles of the nose, or mucous membranes. (2)
- Clindamycin phosphate and tretinoin gel is not for oral, ophthalmic, or intravaginal use. (2)

3 DOSAGE FORMS AND STRENGTHS

Topical gel: Clindamycin phosphate, USP 1.2% and tretinoin, USP 0.025% gel in 30 and 60 gram tubes. (3)

4 CONTRAINDICATIONS

Clindamycin phosphate and tretinoin gel is contraindicated in patients with regional enteritis, ulcerative colitis, or history of antibiotic–associated colitis. (4)

5 WARNINGS AND PRECAUTIONS

- Colitis: Clindamycin can cause severe colitis, which may result in death. Diarrhea, bloody diarrhea, and colitis (including pseudomembranous colitis) have been reported with the use of clindamycin. Clindamycin phosphate and tretinoin gel should be discontinued if significant diarrhea occurs. (5.1)
- Ultraviolet Light and Environmental Exposures: Avoid exposure to sunlight and sunlamps. Wear sunscreen daily. (5.2)

6 ADVERSE REACTIONS

Observed local adverse reactions in patients treated with clindamycin phosphate and tretinoin gel were skin erythema, scaling, itching, burning, and stinging. Other most commonly reported adverse events (≥ 1% in patients treated with clindamycin phosphate and tretinoin gel) were nasopharyngitis, pharyngolaryngeal pain, dry skin, cough, and sinusitis. (6.1)

To report SUSPECTED ADVERSE REACTIONS, contact Teva at 1-888-838-2872 or FDA at 1-800-FDA-1088 or www.fda.gov/medwatch.

7 DRUG INTERACTIONS

- Concomitant use of topical medications with a strong drying effect can increase skin irritation. Use with caution. (7.1)
- Clindamycin phosphate and tretinoin gel should not be used in combination with erythromycin-containing products because of its clindamycin component. (7.2)

FULL PRESCRIBING INFORMATION

1 INDICATIONS AND USAGE

Clindamycin phosphate and tretinoin gel 1.2% / 0.025% is indicated for the topical treatment of acne vulgaris in patients 12 years or older.

2 DOSAGE AND ADMINISTRATION

At bedtime, squeeze a pea-sized amount of medication onto one fingertip, dot onto the chin, cheeks, nose, and forehead, then gently rub over the entire face. Clindamycin phosphate and tretinoin gel should be kept away from the eyes, the mouth, angles of the nose, and mucous membranes.

Clindamycin phosphate and tretinoin gel is not for oral, ophthalmic, or intravaginal use.

3 DOSAGE FORMS AND STRENGTHS

Clindamycin phosphate and tretinoin gel, a combination of a lincosamide antibiotic and a retinoid, contains clindamycin phosphate, USP 1.2% and tretinoin, USP 0.025%, formulated as a topical gel. Each gram of clindamycin phosphate and tretinoin gel contains, as dispensed, 10 mg (1%) clindamycin as phosphate, USP, and 0.25 mg (0.025%) tretinoin, USP in an aqueous based gel. Clindamycin phosphate and tretinoin gel is available in 30 gram and 60 gram tubes.

4 CONTRAINDICATIONS

Clindamycin phosphate and tretinoin gel is contraindicated in patients with regional enteritis, ulcerative colitis, or history of antibiotic-associated colitis.

5 WARNINGS AND PRECAUTIONS

5.1 Colitis

Systemic absorption of clindamycin has been demonstrated following topical use of this product. Diarrhea, bloody diarrhea, and colitis (including pseudomembranous colitis) have been reported with the use of topical clindamycin. When significant diarrhea occurs, clindamycin phosphate and tretinoin gel should be discontinued.

Severe colitis has occurred following oral or parenteral administration of clindamycin with an onset of up to several weeks following cessation of therapy. Antiperistaltic agents such as opiates and diphenoxylate with atropine may prolong and/or worsen severe colitis. Severe colitis may result in death.

Studies indicate a toxin(s) produced by clostridia is one primary cause of antibiotic-associated colitis. The colitis is usually characterized by severe persistent diarrhea and severe abdominal cramps and may be associated with the passage of blood and mucus. Stool cultures for Clostridium difficile and stool assay for C. difficile toxin may be helpful diagnostically.

5.2 Ultraviolet Light and Environmental Exposure

Exposure to sunlight, including sunlamps, should be avoided during the use of clindamycin phosphate and tretinoin gel, and patients with sunburn should be advised not to use the product until fully recovered because of heightened susceptibility to sunlight as a result of the use of tretinoin. Patients who may be required to have considerable sun exposure due to occupation and those with inherent sensitivity to the sun should exercise particular caution. Daily use of sunscreen products and protective apparel (e.g., a hat) are recommended. Weather extremes, such as wind or cold, also may be irritating to patients under treatment with clindamycin phosphate and tretinoin gel.

6 ADVERSE REACTIONS

6.1 Clinical Studies Experience

Because clinical trials are conducted under prescribed conditions, adverse reaction rates observed in the clinical trial may not reflect the rates observed in practice. The adverse reaction information from clinical trials does, however, provide a basis for identifying the adverse reactions that appear to be related to drug use for approximating rates.

The safety data presented in Table 1 (below) reflects exposure to clindamycin phosphate and tretinoin gel in 1,853 patients with acne vulgaris. Patients were 12 years and older and were treated once daily for 12 weeks. Adverse reactions that were reported in ≥ 1% of patients treated with clindamycin phosphate and tretinoin gel were compared to adverse reactions in patients treated with clindamycin phosphate 1.2% in vehicle gel, tretinoin 0.025% in vehicle gel, and the vehicle gel alone:

Table 1: Adverse Reactions Reported in at Least 1% of Patients Treated with Clindamycin Phosphate and Tretinoin Gel: 12-Week Studies
 | Clindamycin
 | Phosphate and
 | Tretinoin Gel | Clindamycin | Tretinoin | Vehicle
 | N=1853 | N=1428 | N=846 | N=423
 | N (%) | N (%) | N (%) | N (%)
PATIENTS WITH AT LEAST ONE AR | 497 (27) | 342 (24) | 225 (27) | 91 (22)
Nasopharyngitis | 65 (4) | 64 (5) | 16 (2) | 5 (1)
Pharyngolaryngeal pain | 29 (2) | 18 (1) | 5 (1) | 7 (2)
Dry skin | 23 (1) | 7 (1) | 3 (<1) | 0 (0)
Cough | 19 (1) | 21 (2) | 9 (1) | 2 (1)
Sinusitis | 19 (1) | 19 (1) | 15 (2) | 4 (1)
Note: Formulations used in all treatment arms were in the clindamycin phosphate and tretinoin vehicle gel.

Cutaneous safety and tolerance evaluations were conducted at each study visit in all of the clinical trials by assessment of erythema, scaling, itching, burning, and stinging:

Table 2: Clindamycin Phosphate and Tretinoin Gel-Treated Patients with Local Skin Reactions
Local Reaction | Baseline | End of Treatment
 | N=1835 | N=1614
 | N (%) | N (%)
Erythema | 636 (35) | 416 (26)
Scaling | 237 (13) | 280 (17)
Itching | 189 (10) | 70 (4)
Burning | 38 (2) | 56 (4)
Stinging | 33 (2) | 27 (2)

At each study visit, application site reactions on a scale of 0 (none), 1 (mild), 2 (moderate), and 3 (severe), and the mean scores were calculated for each of the local skin reactions. In Studies 1 and 2, 1277 subjects enrolled with moderate to severe acne, 854 subjects treated with clindamycin phosphate and tretinoin gel and 423 treated with vehicle. Analysis over the twelve week period demonstrated that cutaneous irritation scores for erythema, scaling, itching, burning, and stinging peaked at two weeks of therapy, and were slightly higher for the clindamycin phosphate and tretinoin-treated group, decreasing thereafter.

One open-label 12-month safety study for clindamycin phosphate and tretinoin gel showed a similar adverse reaction profile as seen in the 12-week studies. Eighteen out of 442 subjects (4%) reported gastrointestinal symptoms.

7 DRUG INTERACTIONS

7.1 Concomitant Topical Medication

Concomitant topical medication, medicated or abrasive soaps and cleansers, soaps and cosmetics that have a strong drying effect, and products with high concentrations of alcohol, astringents, spices or lime should be used with caution. When used with clindamycin phosphate and tretinoin gel, there may be increased skin irritation.

7.2 Erythromycin

Clindamycin phosphate and tretinoin gel should not be used in combination with erythromycin-containing products due to its clindamycin component. In vitro studies have shown antagonism between these two antimicrobials. The clinical significance of this in vitro antagonism is not known.

7.3 Neuromuscular Blocking Agents

Clindamycin has been shown to have neuromuscular blocking properties that may enhance the action of other neuromuscular blocking agents. Therefore, clindamycin phosphate and tretinoin gel should be used with caution in patients receiving such agents.

8 USE IN SPECIFIC POPULATIONS

8.1 Pregnancy

Pregnancy Category C. There are no well-controlled trials in pregnant women treated with clindamycin phosphate and tretinoin gel. Clindamycin phosphate and tretinoin gel should be used during pregnancy only if the potential benefit justifies the potential risk to the fetus. Clindamycin phosphate and tretinoin gel was tested for maternal and developmental toxicity in New Zealand White Rabbits with topical doses of 60, 180 and 600 mg/kg/day. Clindamycin phosphate and tretinoin gel at 600 mg/kg/day (approximately 12 times the recommended clinical dose assuming 100% absorption and based on body surface area comparison) was considered to be the no-observed-adverse-effect level (NOAEL) for maternal and developmental toxicity following dermal administration of clindamycin phosphate and tretinoin gel for two weeks prior to artificial insemination and continuing until gestation day 18, inclusive. For purposes of comparisons of the animal exposure to human exposure, the recommended clinical dose is defined as 1 g of clindamycin phosphate and tretinoin gel applied daily to a 60 kg person.

Clindamycin

Teratology (Segment II) studies using clindamycin were performed orally in rats (up to 600 mg/kg/day) and mice (up to 100 mg/kg/day) (583 and 49 times amount of clindamycin in the recommended clinical dose based on a body surface area comparison, respectively) or with subcutaneous doses of clindamycin up to 180 mg/kg/day (175 and 88 times the amount of clindamycin in the recommended clinical dose based on a body surface area comparison, respectively) revealed no evidence of teratogenicity.

Tretinoin

In oral Segment III studies in rats with tretinoin, decreased survival of neonates and growth retardation were observed at doses in excess of 2 mg/kg/day (~ 78 times the recommended clinical dose assuming 100% absorption and based on body surface area comparison).

With widespread use of any drug, a small number of birth defect reports associated temporally with the administration of the drug would be expected by chance alone. Thirty cases of temporally associated congenital malformations have been reported during two decades of clinical use of another formulation of topical tretinoin. Although no definite pattern of teratogenicity and no causal association have been established from these cases, 5 of the reports describe the rare birth defect category, holoprosencephaly (defects associated with incomplete midline development of the forebrain). The significance of these spontaneous reports in terms of risk to the fetus is not known.

Dermal tretinoin has been shown to be fetotoxic in rabbits when administered in doses 40 times the recommended human clinical dose based on a body surface area comparison. Oral tretinoin has been shown to be fetotoxic in rats when administered in doses 78 times the recommended clinical dose based on a body surface area comparison.

8.3 Nursing Mothers

It is not known whether clindamycin is excreted in human milk following use of clindamycin phosphate and tretinoin gel. However, orally and parenterally administered clindamycin has been reported to appear in breast milk. Because of the potential for serious adverse reactions in nursing infants, a decision should be made whether to discontinue nursing or to discontinue the drug, taking into account the importance of the drug to the mother. It is not known whether tretinoin is excreted in human milk. Because many drugs are excreted in human milk, caution should be exercised when clindamycin phosphate and tretinoin gel is administered to a nursing woman.

8.4 Pediatric Use

Safety and effectiveness of clindamycin phosphate and tretinoin gel in pediatric patients under the age of 12 have not been established.

Clinical trials of clindamycin phosphate and tretinoin gel included patients 12 to 17 years of age. [See Clinical Studies (14)]

8.5 Geriatric Use

Clinical studies of clindamycin phosphate and tretinoin gel did not include sufficient numbers of subjects aged 65 and over to determine whether they respond differently from younger subjects.

11 DESCRIPTION

Clindamycin phosphate and tretinoin gel 1.2% / 0.025%, is an antibiotic and retinoid combination gel product with two active ingredients. Clindamycin phosphate, USP is a water-soluble ester of the semi-synthetic antibiotic produced by a 7(S)-chloro-substitution of the 7(R)-hydroxyl group of the parent antibiotic lincomycin.

The chemical name for clindamycin phosphate, USP is Methyl 7-chloro-6,7,8-trideoxy-6-(1-methyl-trans-4- propyl-L-2-pyrrolidinecarboxamido)-1-thio-L-threo-α-D-galacto-octopyranoside 2-(dihydrogen phosphate). The structural formula for clindamycin phosphate, USP is represented below:

Clindamycin phosphate, USP:

Molecular Formula: C18H34ClN2O8PS Molecular Weight: 504.97

The chemical name for tretinoin, USP is 3,7-Dimethyl-9-(2,6,6-trimethyl-1-cyclohexen-1-yl)-2,4,6,8- nonatetraenoic acid (all-trans form). The structural formula for tretinoin, USP is represented below:

Tretinoin, USP:

Molecular Formula: C20H28O2 Molecular Weight: 300.44

Clindamycin phosphate and tretinoin gel 1.2% / 0.025% contains the following inactive ingredients: anhydrous citric acid, butylated hydroxytoluene, edetate disodium, hydroxyethyl cellulose, glycerin, methylparaben, polysorbate 80, propylparaben, purified water, tromethamine and xanthan gum.

12 CLINICAL PHARMACOLOGY

12.1 Mechanisms of Action

Clindamycin

[see Microbiology (12.4)].

Tretinoin

Although the exact mode of action of tretinoin is unknown, current evidence suggests that topical tretinoin decreases cohesiveness of follicular epithelial cells with decreased microcomedo formation. Additionally, tretinoin stimulates mitotic activity and increased turnover of follicular epithelial cells causing extrusion of the comedones.

12.3 Pharmacokinetics

In an open-label, multiple-dose study treating 12 subjects with moderate to severe acne, the percutaneous absorption of tretinoin following 14 consecutive daily applications of approximately 4 g of clindamycin phosphate and tretinoin gel was minimal. Quantifiable tretinoin plasma concentrations ranged from 1.0 to 1.6 ng/mL, with unquantifiable plasma concentrations in 50% to 92% of subjects at any given timepoint following administration. The plasma concentrations of the key tretinoin metabolites, 13- cis -retinoic acid and 4-oxo-13-cis-retinoic acid, ranged from 1.0 to 1.4 ng/mL and from 1.6 to 6.5 ng/mL, respectively. Plasma concentrations for clindamycin generally did not exceed 3.5 ng/mL, with the exception of one subject whose plasma concentration reached 13.1 ng/mL.

12.4 Microbiology

Clindamycin binds to the 50S ribosomal subunits of susceptible bacteria and prevents elongation of peptide chains by interfering with peptidyl transfer, thereby suppressing bacterial protein synthesis. Clindamycin has been shown to have in vitro activity against Propionibacterium acnes, an organism which has been associated with acne vulgaris; however, the clinical significance of this activity against P. acnes was not examined in clinical trials with clindamycin phosphate and tretinoin gel. P acnes resistance to clindamycin has been documented. Resistance to clindamycin is often associated with resistance to erythromycin.

13 NONCLINICAL TOXICOLOGY

13.1 Carcinogenesis, Mutagenesis, Impairment of Fertility

Carcinogenicity, mutagenicity and impairment of fertility testing of clindamycin phosphate and tretinoin gel have not been performed in any species.

Clindamycin

The carcinogenicity of a 1% clindamycin phosphate gel similar to clindamycin phosphate and tretinoin gel was evaluated by daily application to mice for two years. The daily doses used in this study were approximately 13 and 72 times higher than the human dose of clindamycin phosphate from clindamycin phosphate and tretinoin gel, assuming complete absorption and based on a body surface area comparison. No significant increase in tumors was noted in the treated animals. For purposes of comparisons of the animal exposure to human exposure, the recommended human topical clinical dose is defined as 1 g of clindamycin phosphate and tretinoin gel applied daily to a 60 kg person.

Fertility (Segment 1) studies in rats treated orally with up to 300 mg/kg/day of clindamycin (approximately 290 times the amount of clindamycin delivered from the recommended clinical dose for clindamycin phosphate and tretinoin gel, based on a body surface area comparison) revealed no effects on fertility or mating ability.

Tretinoin

In two independent studies with long-term topical application of tretinoin in mice, carcinogenicity was not observed. In both studies, tretinoin was administered topically (0.025% or 0.1%) three times per week for up to two years. No carcinogenicity was observed with maximum effects of dermal amyloidosis in the basal layer of the skin.

Tretinoin has been shown to enhance photoco-carcinogenicity in properly performed specific studies, employing concurrent or intercurrent exposure to the drug and UV radiation. The contribution of clindamycin to that effect is unknown. Although the significance of these studies to humans is not clear, patients should minimize exposure to sun.

The genotoxic potential of tretinoin was evaluated in an in vitro Ames Salmonella reversion test and an in vitro chromosomal aberration assay in Chinese hamster ovary cells. Both tests were negative.

In oral Segment 1 studies in rats treated with tretinoin, the no-observed-effect-level was 2 mg/kg/day (~78 times the recommended clinical dose assuming 100% absorption and based on body surface area comparison).

14 CLINICAL STUDIES

The safety and efficacy of once daily use of clindamycin phosphate and tretinoin gel for treatment of acne vulgaris were assessed in three 12-week prospective, multi-center, randomized, blinded studies in patients 12 years and older. Studies 1 and 2 were of identical design, and compared clindamycin phosphate and tretinoin gel to clindamycin in the vehicle gel, tretinoin in the vehicle gel, and the vehicle gel alone. Patients with mild, moderate, or severe acne were enrolled in the studies. The co-primary efficacy variables were:

(1) Mean percent change from baseline at Week 12 in

- inflammatory lesion counts,
- non-inflammatory lesion counts, and
- total lesion counts

(2) Percent of subjects who cleared or almost cleared at Week 12 as judged by an Evaluator’s Global Severity (EGS) score.

The EGS scoring scale used in all of the clinical trials for clindamycin phosphate and tretinoin gel is as follows:

Grade | Description
Clear | Normal, clear skin with no evidence of acne vulgaris
Almost Clear | Rare non-inflammatory lesions present, with rare non-inflamed papules (papules must be resolving and may be hyperpigmented, though not pink-red)
Mild | Some non-inflammatory lesions are present, with few inflammatory lesions (papules/pustules only; no nodulocystic lesions)
Moderate | Non-inflammatory lesions predominate, with multiple inflammatory lesions evident: several to many comedones and papules/pustules, and there may or may not be one small nodulo-cystic lesion
Severe | Inflammatory lesions are more apparent many comedones and papules/pustules, there may or may not be a few nodulocystic lesions
Very Severe | Highly inflammatory lesions predominate, variable number of comedones, many papules/pustules and many nodulocystic lesions

In Study 1, a total of 1,252 patients were enrolled, and in Study 2, a total of 1,288 patients were enrolled. The combined results are presented in Table 3.

Table 3: Efficacy Results at Week 12 in Studies 1 and 2.
 | Clindamycin
 | Phosphate and | Clindamycin | Tretinoin | Vehicle
 | Tretinoin Gel
 | N=845 | N=426 | N=846 | N=423
Evaluator’s Global Severity: N (%)
Patients achieving success* | 180 (21%) | 70 (16%) | 122 (14%) | 34 (8%)
Inflammatory Lesion Count (% reduction from baseline)
Mean | 48% | 42% | 39% | 26%
Non-inflammatory Lesion Count (% reduction from baseline)
Mean | 36% | 27% | 31% | 16%
Total Lesion Count (% reduction from baseline)
Mean | 41% | 34% | 34% | 20%
* Success was defined as cleared or almost cleared at Week 12

In Study 3, clindamycin phosphate and tretinoin gel was compared to clindamycin gel in a total of 2,010 patients with moderate or severe acne vulgaris (see Table 3). As with Studies 1 and 2, the co-primary endpoints were mean percent reduction in lesion counts (inflammatory, non-inflammatory and total) and the Evaluator’s Global Severity score. In Study 3, success on the EGS score was assessed by the percentage of subjects who had at least 2 grades of improvement from Baseline to Week 12.

Table 4: Efficacy Results at Week 12 in Study 3
 | Clindamycin Phosphate and
 | Tretinoin Gel | Clindamycin
 | N = 1008 | N = 1002
Evaluator’s Global Severity: N (%)
Patients achieving success* | 415 (41%) | 345 (34%)
Inflammatory Lesion Count (% reduction from baseline)
Mean | 61% | 55%
Non-inflammatory Lesion Count (% reduction from baseline)
Mean | 50% | 41%
Total Lesion Count (% reduction from baseline)
Mean | 54% | 47%
* Success was defined as at least a 2-grade improvement at Week 12 from baseline.

16 HOW SUPPLIED/STORAGE AND HANDLING

Clindamycin phosphate and tretinoin gel 1.2% / 0.025% is supplied as follows:

30 gram tube NDC 0472-1790-30

60 gram tube NDC 0472-1790-60

Storage and Handling

Store at 25°C (77°F); excursions permitted to 15 to 30°C (59 to 86°F) [see USP Controlled Room Temperature]. Protect from light. Protect from freezing. Keep away from heat.

Keep tube tightly closed.

Keep out of the reach of children.

17 PATIENT COUNSELING INFORMATION

See FDA-Approved Patient Labeling (17.4).

17.1 Instructions for Use

- At bedtime, the face should be gently washed with a mild soap and warm water. After patting the skin dry, apply clindamycin phosphate and tretinoin gel as a thin layer over the entire face (excluding the eyes and lips).
- Patients should be advised not to use more than the recommended pea sized amount and not to apply more often than once daily (at bedtime) as this will not make for faster results and may increase irritation.
- A sunscreen should be applied every morning and reapplied over the course of the day as needed. Patients should be advised to avoid exposure to sunlight, sunlamp, ultraviolet light, and other medicines that may increase sensitivity to sunlight.

17.2 Skin Irritation

Clindamycin phosphate and tretinoin gel may cause irritation such as erythema, scaling, itching, burning, or stinging.

17.3 Colitis

In the event a patient treated with clindamycin phosphate and tretinoin gel experiences severe diarrhea or gastrointestinal discomfort, clindamycin phosphate and tretinoin gel should be discontinued and a physician should be contacted.

Manufactured For:
Teva Pharmaceuticals
Parsippany, NJ 07054

Rev. B 2/2023

PATIENT INFORMATION

Clindamycin Phosphate and Tretinoin (klinʺ da myeʹ sin fosʹ fate and tretʹ i noyn)
Gel 1.2% / 0.025%

IMPORTANT: Not for mouth, eye, or vaginal use.

Read the Patient Information that comes with clindamycin phosphate and tretinoin gel before you start using it and each time you get a refill. There may be new information. This leaflet does not take the place of talking with your doctor about your acne or treatment.

What is clindamycin phosphate and tretinoin gel?

Clindamycin phosphate and tretinoin gel is an antibiotic and retinoid combination medicine used for the skin treatment of acne in patients 12 years and older.

Who should not use clindamycin phosphate and tretinoin gel?

Do not use clindamycin phosphate and tretinoin gel if you:

- have Crohn’s Disease
- have Ulcerative Colitis
- have developed colitis with past antibiotic use

Tell your doctor:

- if you are pregnant or planning to become pregnant. It is not known if clindamycin phosphate and tretinoin gel may harm your unborn baby.
- if you are breastfeeding. Clindamycin phosphate and tretinoin gel may pass through your milk and may harm your baby.
- about all the medicines and skin products you use:
  - Clindamycin phosphate and tretinoin gel should not be used with erythromycin-containing products.
  - Avoid medicated or abrasive soaps and cleansers, soaps and cosmetics that have a strong drying effect, and skin products that contain alcohol, astringents, spices or lime. These products may cause increased skin irritation if used with clindamycin phosphate and tretinoin gel.

How should I use clindamycin phosphate and tretinoin gel?

Use clindamycin phosphate and tretinoin gel exactly as prescribed. It may take some time for you to see improvement of your acne with clindamycin phosphate and tretinoin gel. Your doctor will tell you how long to use clindamycin phosphate and tretinoin gel.

At bedtime:

- Wash your face gently with a mild soap and warm water.
- Pat the skin dry.
- Apply a pea-size amount of clindamycin phosphate and tretinoin gel to your fingertip and spread it over your face. Gently, smooth it into your skin. Do not get clindamycin phosphate and tretinoin gel in your eyes or mouth, on your lips, on the corners of your nose, or on open wounds.

In the morning:

- Apply a sunscreen and reapply during the day as needed.
- Do not apply clindamycin phosphate and tretinoin gel more than once a day
- Do not use too much clindamycin phosphate and tretinoin gel. Too much clindamycin phosphate and tretinoin gel may irritate your skin.
- Do not wash your face more than 2 to 3 times a day. Washing your face too often or scrubbing it may make your acne worse.

Avoid:

- excessive exposure to the sun, cold, and wind. Weather extremes can dry and burn the skin. Always use a sunscreen on clindamycin phosphate and tretinoin gel treated skin, even on cloudy days. Use other protective clothing such as a hat when you are in the sun.
- the use of sunlamps and tanning booths

If your face becomes sunburned, stop clindamycin phosphate and tretinoin gel until your skin has healed.

What are possible side effects with clindamycin phosphate and tretinoin gel?

- Skin irritation. Clindamycin phosphate and tretinoin gel may cause skin irritation such as dryness, redness, peeling, burning, or stinging. Stop clindamycin phosphate and tretinoin gel and call your doctor if your skin becomes very red, swollen, blistered, or crusted.
- Change in skin color. Clindamycin phosphate and tretinoin gel may cause a temporary skin color change (lighter or darker).
- Colitis. This occurs rarely. Stop clindamycin phosphate and tretinoin gel and call your doctor if you develop severe watery diarrhea, or bloody diarrhea.

Talk to your doctor about any side effect that bothers you or that does not go away.

These are not all the side effects with clindamycin phosphate and tretinoin gel. Ask your doctor or pharmacist for more information.

How should I store clindamycin phosphate and tretinoin gel?

- Store clindamycin phosphate and tretinoin gel at room temperature, 59 to 86°F (15 to 30°C). Do not freeze.
- Keep clindamycin phosphate and tretinoin gel away from heat and light.
- Keep the tube tightly closed.
- Keep clindamycin phosphate and tretinoin gel and all medicines out of the reach of children.

General information about clindamycin phosphate and tretinoin gel

Medicines are sometimes prescribed for purposes other than those listed in patient information leaflet. Do not use clindamycin phosphate and tretinoin gel for a condition for which it was not prescribed. Do not give clindamycin phosphate and tretinoin gel to other people, even if they have the same symptoms you have. It may harm them.

This leaflet summarizes the most important information about clindamycin phosphate and tretinoin gel. If you would like more information, talk with your doctor. You can also ask your pharmacist or doctor for information about clindamycin phosphate and tretinoin gel that is written for healthcare professionals.

If you have questions about clindamycin phosphate and tretinoin gel you can also call Teva at 1-888-838-2872.

What are the ingredients in clindamycin phosphate and tretinoin gel?

Active Ingredients: clindamycin phosphate, USP 1.2% and tretinoin, USP 0.025%

Inactive Ingredients: anhydrous citric acid, butylated hydroxytoluene, edetate disodium, hydroxyethyl cellulose, glycerin, methylparaben, polysorbate 80, propylparaben, purified water, tromethamine and xanthan gum.

Manufactured For:
Teva Pharmaceuticals
Parsippany, NJ 07054

Rev. B 2/2023

PACKAGE LABEL.PRINCIPAL DISPLAY PANEL

NDC 0472-1790-30

Clindamycin Phosphate and Tretinoin Gel

1.2%/0.025%

PHARMACIST: Dispense the accompanying Patient Information Leaflet to each patient.

FOR TOPICAL USE ONLY. NOT FOR OPHTHALMIC, ORAL, OR INTRAVAGINAL USE.

NET WT. 30 g

Rx Only